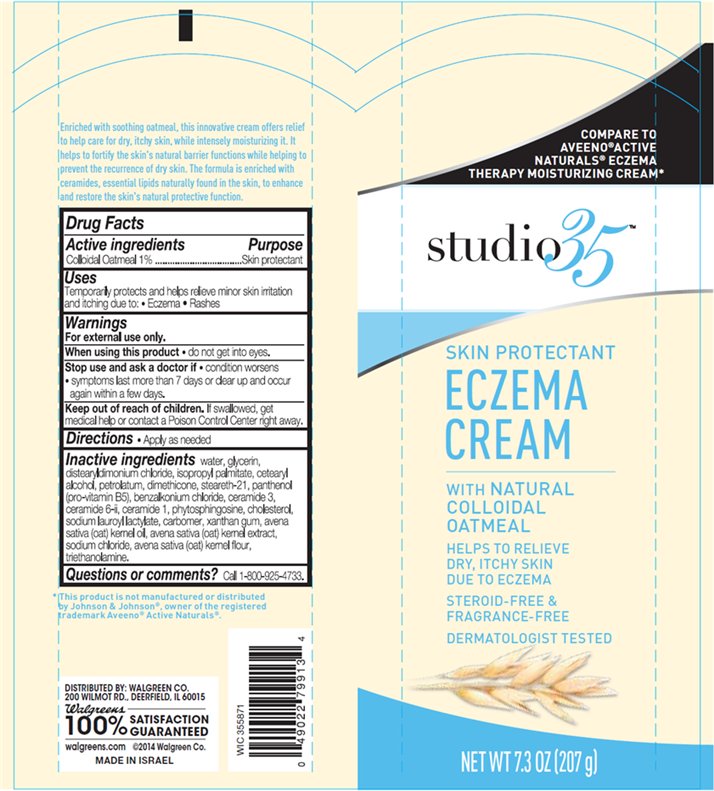 DRUG LABEL: studio35 Eczema
NDC: 0363-4246 | Form: CREAM
Manufacturer: Walgreen Company
Category: otc | Type: HUMAN OTC DRUG LABEL
Date: 20140910

ACTIVE INGREDIENTS: OATMEAL 1 g/100 g
INACTIVE INGREDIENTS: WATER; GLYCERIN; DISTEARYLDIMONIUM CHLORIDE; ISOPROPYL PALMITATE; CETOSTEARYL ALCOHOL; PETROLATUM; DIMETHICONE; STEARETH-21; PANTHENOL; BENZALKONIUM CHLORIDE; SODIUM CHLORIDE; CERAMIDE 3; CERAMIDE 6 II; CERAMIDE 1; PHYTOSPHINGOSINE; CHOLESTEROL; SODIUM LAUROYL LACTYLATE; XANTHAN GUM; OAT KERNEL OIL; OAT; TROLAMINE

studio35™ Eczema Cream

Active ingredient

Colloidal Oatmeal 1%

Purpose

Skin Protectant

Uses

Temporarily protects and helps relieve minor skin irritation and itching due to:

- Eczema
- Rashes

Warnings

For external use only.

When using this product

- do not get into eyes.

Stop use and ask a doctor if

- conditions worsens
- symptoms last more than 7 days or clear up and occur again within a few days.

Keep Out of Reach of Children.

If swallowed, get medical help or contact a Poison Control Center right away.

Directions

- Apply as needed

Inactive ingredients

water, glycerin, distearyldimonium chloride, isopropyl palmitate, cetearyl alcohol, petrolatum, dimethicone, steareth-21, panthenol (pro-vitamin B5), benzalkonium chloride, ceramide 3, ceramide 6-ii, ceramide 1, phytosphingosine, cholesterol, sodium lauroyl lactylate, carbomer, xanthan gum, avena sativa (oat) kernel oil, avena sativa (oat) kernel extract, sodium chloride, avena sativa (oat) kernel flour, triethanolamine.

Questions or comments?

Call 1-800-925-4733.

Package/Label Principal Display Panel

studio35™

COMPARE TO
AVEENO® ACTIVE
NATURALS® ECZEMA
THERAPY MOISTURIZING CREAM*

SKIN PROTECTANT
ECZEMA
CREAM

WITH NATURAL
COLLOIDAL
OATMEAL

HELPS TO RELIEVE
DRY, ITCHY SKIN
DUE TO ECZEMA

STEROID-FREE &
FRAGRANCE-FREE

DERMATOLOGIST TESTED

NET WT 7.3 OZ (207 g)

Enriched with soothing oatmeal, this innovative cream offers relief
to help care for dry, itchy skin, while intensely moisturizing it. It
helps to fortify the skin's natural barrier functions while helping to
prevent the recurrence of dry skin. The formula is enriched with
ceramides, essential lipids naturally found in the skin, to enhance
and restore the skin's natural protective function.

*This product is not manufactured or distributed
by Johnson & Johnson®, owner of the registered
trademark Aveeno® Active Naturals®.

DISTRIBUTED BY: WALGREEN CO.
200 WILMOT RD., DEERFIELD, IL 60015
100% SATISFACTION GUARANTEED
walgreens.com © 2014 Walgreen Co.
MADE IN ISRAEL

Carton Label